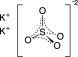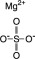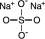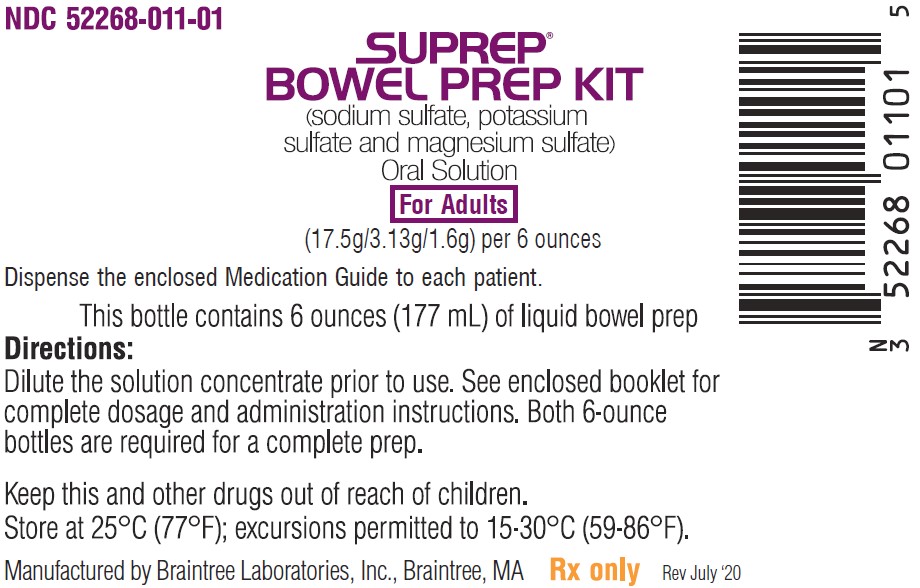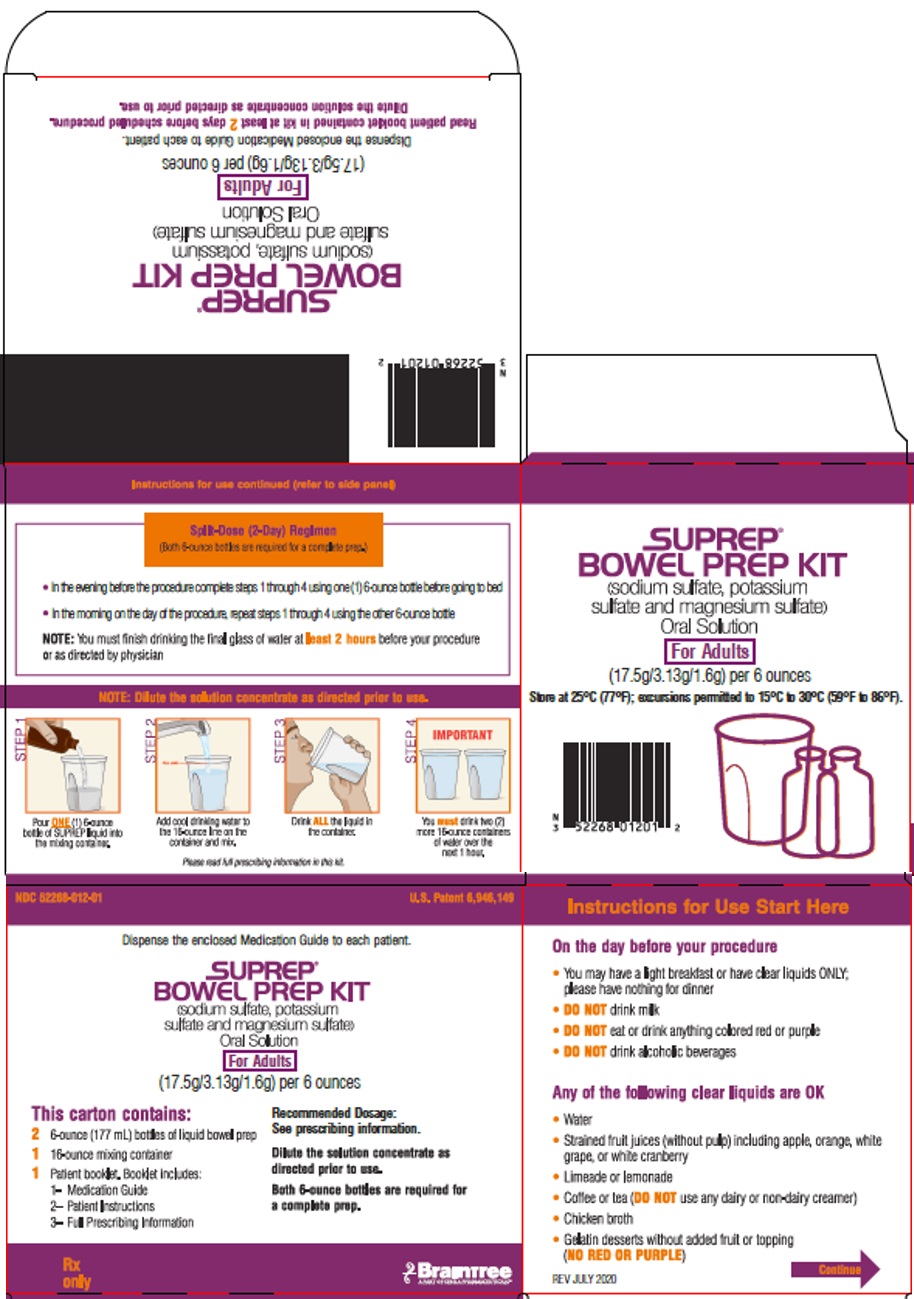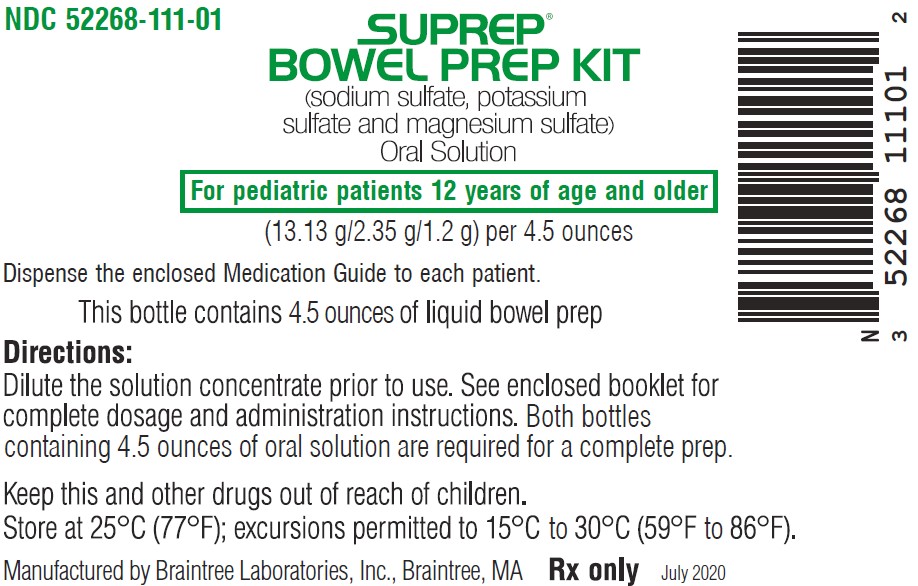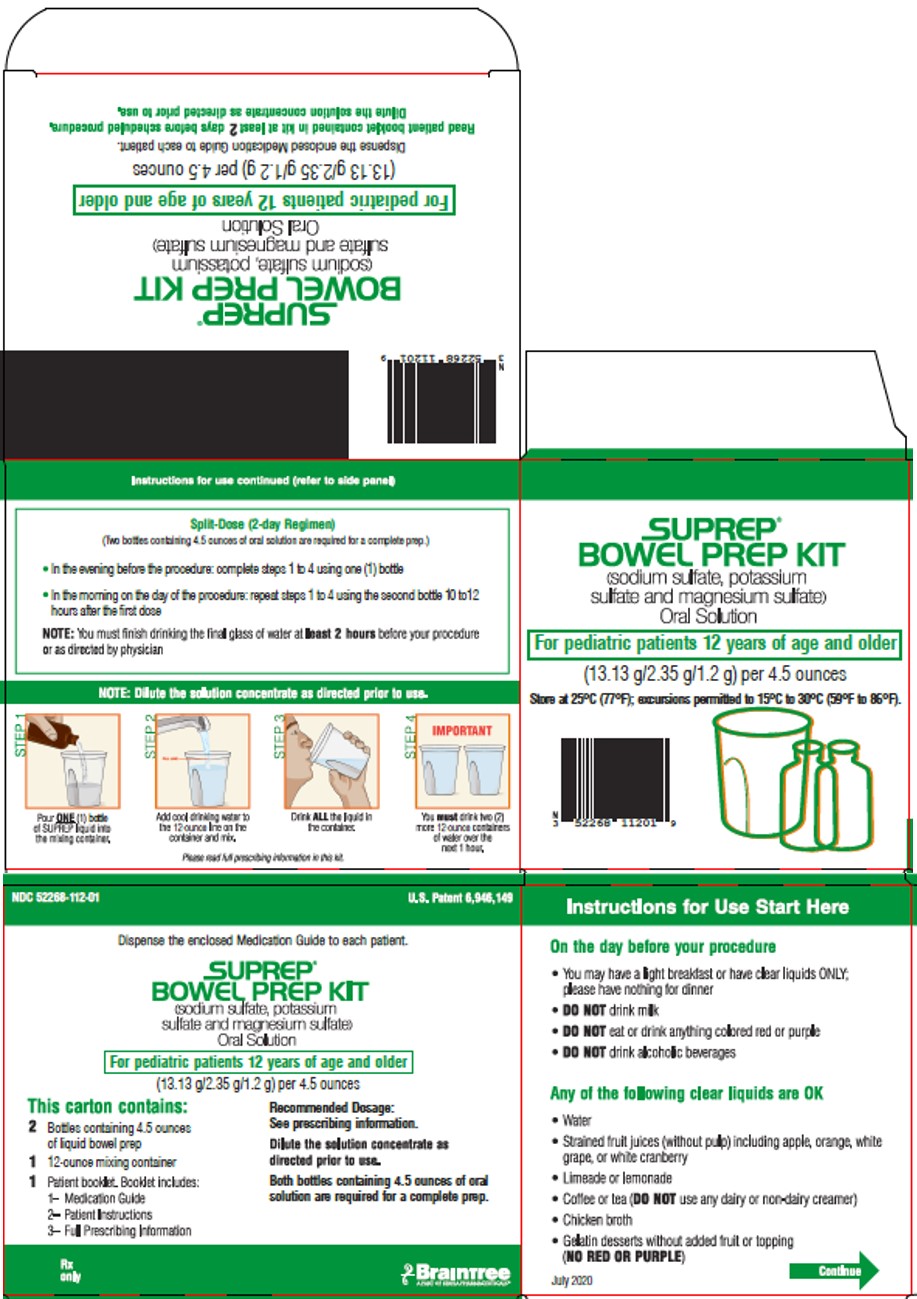 DRUG LABEL: SUPREP Bowel Prep
NDC: 52268-012 | Form: SOLUTION, CONCENTRATE
Manufacturer: Braintree Laboratories, Inc.
Category: prescription | Type: Human Prescription Drug Label
Date: 20251130

ACTIVE INGREDIENTS: SODIUM SULFATE 17.5 g/1 mL; POTASSIUM SULFATE 3.13 g/1 mL; MAGNESIUM SULFATE, UNSPECIFIED FORM 1.6 g/1 mL
INACTIVE INGREDIENTS: SODIUM BENZOATE; SUCRALOSE; MALIC ACID; CITRIC ACID MONOHYDRATE

HIGHLIGHTS OF PRESCRIBING INFORMATION

These highlights do not include all the information needed to use SUPREP BOWEL PREP KIT safely and effectively. See full prescribing information for SUPREP BOWEL PREP KIT.
SUPREP BOWEL PREP KIT (sodium sulfate, potassium sulfate, and magnesium sulfate) oral solution
Initial U.S. Approval: 2010

RECENT MAJOR CHANGES

Warnings and Precautions, Hypersensitivity Reactions (5.8) 11/2025

1 INDICATIONS AND USAGE

SUPREP Bowel Prep Kit is an osmotic laxative indicated for cleansing of the colon in preparation for colonoscopy in adult and pediatric patients 12 years of age and older. (1)

2 DOSAGE AND ADMINISTRATION

Preparation and Administration (2.2)

- Must dilute in water prior to ingestion.
- Administration of two bottles of SUPREP Bowel Prep Kit is required for a complete preparation for colonoscopy. One bottle is equivalent to one
  dose.
- Must consume additional water after each dose.
- Stop consumption of all fluids at least 2 hours before the colonoscopy.

Recommended Dosage and Administration

- Split-Dose (two-day) regimen consists of two doses of SUPREP Bowel Prep Kit: first dose during the evening prior to colonoscopy and second dose the next day, during the morning of colonoscopy. (2.1, 2.3, 2.4)
- Recommended SUPREP Bowel Prep Kit dosage is:
  º Adults: Two 6-ounce doses. (2.3)
  º Pediatric Patients 12 Years of Age and Older: Two 4.5-ounce doses. (2.4)
- For complete information on preparation before colonoscopy and administration of the dosage regimen, see full prescribing Information. (2.1, 2.2, 2.3, 2.4)

3 DOSAGE FORMS AND STRENGTHS

- SUPREP Bowel Prep Kit (for adults): Two bottles each containing 6 ounces of an oral solution of 17.5 grams sodium sulfate, 3.13 grams potassium sulfate, and 1.6 grams magnesium sulfate. (3)
- SUPREP Bowel Prep Kit (for pediatric patients 12 years of age and older): Two bottles each containing 4.5-ounces of an oral solution of 13.13 grams sodium sulfate, 2.35 grams potassium sulfate, and 1.2 grams magnesium sulfate. (3)

4 CONTRAINDICATIONS

- Gastrointestinal obstruction or ileus (4, 5.6)
- Bowel perforation (4, 5.6)
- Toxic colitis or toxic megacolon (4)
- Gastric retention (4)
- Hypersensitivity to any ingredient (4, 5.8)

5 WARNINGS AND PRECAUTIONS

- Risk of fluid and electrolyte abnormalities: Encourage adequate hydration, assess concurrent medications, and consider laboratory assessments prior to and after each use. (5.1, 7.1)
- Cardiac arrhythmias: Consider pre-dose and post-colonoscopy ECGs in patients at increased risk. (5.2)
- Seizures: Use caution in patients with a history of seizures and patients at increased risk of seizures, including medications that lower the seizure threshold. (5.3, 7.1)
- Patients with renal impairment or taking concomitant medications that affect renal function: Use caution, ensure adequate hydration and consider laboratory testing. (5.4, 7.1)
- Suspected GI obstruction or perforation: Rule out the diagnosis before administration. (4, 5.6)
- Patients at risk for aspiration: Observe during administration. (5.7)
- Hypersensitivity reactions, including anaphylaxis: Inform patients to seek immediate medical care if symptoms occur. (5.8)

6 ADVERSE REACTIONS

Most common adverse reactions are:

- Adults (>2%): overall discomfort, abdominal distention, abdominal pain, nausea, and vomiting. (6.1)
- Pediatric Patients (>10%): nausea, abdominal pain, abdominal bloating and vomiting. (6.1)

To report SUSPECTED ADVERSE REACTIONS, contact Braintree Laboratories, Inc. at 1-800-874-6756 or FDA at 1-800-FDA-1088 or www.fda.gov/medwatch.

7 DRUG INTERACTIONS

Drugs that increase risk of fluid and electrolyte imbalance. (7.1)

FULL PRESCRIBING INFORMATION

1 INDICATIONS AND USAGE

SUPREP Bowel Prep Kit is indicated for cleansing of the colon as a preparation for colonoscopy in adult and pediatric patients 12 years of age and older.

2 DOSAGE AND ADMINISTRATION

2.1 Dosage and Administration Overview

Administration of two bottles of SUPREP Bowel Prep Kit and additional water is required for a complete preparation for colonoscopy. One bottle of SUPREP Bowel Prep Kit is equivalent to one dose. SUPREP Bowel Prep Kit is supplied in two dosage strengths [see Dosage Forms and Strengths (3)]. The recommended dosage is:

- Adults: Two 6-ounce doses [see Dosage and Administration (2.3)].
- Pediatric patients 12 years of age and older: Two 4.5-ounce doses [see Dosage and Administration (2.4)].

2.2 Important Preparation and Administration Instructions

- Correct fluid and electrolyte abnormalities before treatment with SUPREP Bowel Prep Kit [see Warnings and Precautions (5.1)]
- Must dilute SUPREP Bowel Prep Kit in water before ingestion.
- Must consume additional water after each dose of SUPREP Bowel Prep Kit.
- On the day before colonoscopy, consume only a light breakfast or clear liquids (e.g., water, strained fruit juice without pulp, lemonade, plain coffee or tea, chicken broth gelatin dessert without fruit). On the day of the colonoscopy only consume clear liquids up to two hours prior to colonoscopy.
- Do not eat solid food or drink milk or eat or drink anything colored red or purple.
- Do not drink alcohol.
- Do not take other laxatives while taking SUPREP Bowel Prep Kit.
- Do not take oral medications within one hour of starting each dose of SUPREP Bowel Prep Kit.
- If taking tetracycline or fluoroquinolone antibiotics, iron, digoxin, chlorpromazine, or penicillamine, take these medications at least 2 hours before and not less than 6 hours after administration of SUPREP Bowel Kit [see Drug Interactions (7.2)].
- Stop consumption of all fluids at least 2 hours prior to the colonoscopy.

2.3 Recommended Dosage and Administration for Adults

The recommended Split-Dose (two-day) regimen for adults consists of two 6-ounce doses of SUPREP Bowel Prep Kit: the first dose during the evening prior to colonoscopy and the second dose the next day, during the morning of the colonoscopy.

Each dose consists of one bottle of SUPREP Bowel Prep Kit with additional water. The total volume of liquid required for colon cleansing (using two bottles) is 3 quarts. The following are recommended dosage and administration instructions for adults:

Dose 1 – On the Day Prior to Colonoscopy:

- May consume a light breakfast, or only clear liquids (no solid food).
- In the evening before the procedure, pour the contents of one bottle of SUPREP Bowel Prep Kit into the mixing container provided.
- Add cool drinking water to the 16-ounce fill line on the container, mix, and drink the entire amount.
- Drink two additional containers filled with water to the 16-ounce fill line over the next hour.

Dose 2 - Day of Colonoscopy:

- Continue to consume only clear liquids.
- In the morning (10 to 12 hours after the evening dose) on the day of the procedure, pour the contents of the second bottle of SUPREP Bowel Prep Kit into the mixing container provided.
- Add cool drinking water to the 16-ounce fill line on the container, mix, and drink the entire amount.
- Drink two additional containers filled with water to the 16-ounce fill line over the next hour.
- Complete all solution of SUPREP Bowel Prep Kit and required water at least two hours prior to colonoscopy.

2.4 Recommended Dosage and Administration for Pediatric Patients 12 Years of Age and Older

The recommended Split-Dose (two-day) regimen for pediatric patients 12 years of age and older consists of two 4.5-ounce doses of SUPREP Bowel Prep Kit: the first dose during the evening prior to colonoscopy and the second dose the next day, during the morning of the colonoscopy.
Each dose consists of one bottle of SUPREP Bowel Prep Kit with additional water. The total volume of liquid required for colon cleansing (using two bottles) is 2.25 quarts. The following are recommended dosage and administration instructions for pediatric patients 12 years of age and older and/or their caregivers:
Dose 1 – On the Day Prior to Colonoscopy:

- May consume a light breakfast, or only clear liquids (no solid food).
- In the evening before the procedure, pour the contents of one bottle of SUPREP Bowel Prep Kit into the mixing container provided.
- Add cool drinking water to the 12-ounce fill line on the container, mix, and drink the entire amount.
- Drink two additional containers filled with water to the 12-ounce fill line over the next hour.

Dose 2 - Day of Colonoscopy:

- Continue to consume only clear liquids.
- In the morning (10 to 12 hours after the evening dose) on the day of the procedure, pour the contents of the second bottle of SUPREP Bowel Prep Kit into the mixing container provided.
- Add cool drinking water to the 12-ounce fill line on the container, mix, and drink the entire amount.
- Drink two additional containers filled with water to the 12-ounce fill line over the next hour.
- Complete all solution of SUPREP Bowel Prep Kit solution and required water at least two hours prior to colonoscopy.

3 DOSAGE FORMS AND STRENGTHS

- SUPREP Bowel Prep Kit (for adults): Two bottles each containing 6 ounces of an oral solution of 17.5 grams sodium sulfate, 3.13 grams potassium sulfate, and 1.6 grams magnesium sulfate as a clear to slightly hazy liquid.

- SUPREP Bowel Prep Kit (for pediatric patients 12 years of age and older): Two bottles each containing 4.5 ounces of an oral solution of 13.13 grams sodium sulfate, 2.35 grams potassium sulfate, and 1.2 grams magnesium sulfate as a clear to slightly hazy liquid.

When diluted as directed, the solution is clear and colorless.

4 CONTRAINDICATIONS

SUPREP Bowel Prep Kit is contraindicated in the following conditions:

- Gastrointestinal obstruction or ileus [see Warnings and Precautions (5.6)]
- Bowel perforation [see Warnings and Precaution (5.6)]
- Toxic colitis or toxic megacolon
- Gastric retention
- Hypersensitivity to any of the ingredients in SUPREP Bowel Prep Kit [see Warnings and Precautions (5.8) and Description (11)]

5 WARNINGS AND PRECAUTIONS

5.1 Serious Fluid and Serum Chemistry Abnormalities

Advise all patients to hydrate adequately before, during, and after the use of SUPREP Bowel Prep Kit. If a patient develops significant vomiting or signs of dehydration after taking SUPREP Bowel Prep Kit, consider performing post-colonoscopy lab tests (electrolytes, creatinine, and BUN).

Fluid and electrolyte disturbances can lead to serious adverse events including cardiac arrhythmias, seizures and renal impairment. Correct fluid and electrolyte abnormalities before treatment with SUPREP Bowel Prep Kit. Use SUPREP Bowel Prep Kit with caution in patients with conditions, or who are using medications, that increase the risk for fluid and electrolyte disturbances or may increase the risk of adverse events of seizure, arrhythmias, and renal impairment [see Drug Interactions (7.1)].

SUPREP Bowel Prep Kit can cause temporary elevations in uric acid [see Adverse Reactions (6.1)]. Uric acid fluctuations in patients with gout may precipitate an acute flare. The potential for uric acid elevation should be considered before administering SUPREP Bowel Prep Kit to patients with gout or other disorders of uric acid metabolism.

5.2 Cardiac Arrhythmias

There have been rare reports of serious arrhythmias associated with the use of ionic osmotic laxative products for bowel preparation. Use caution when prescribing SUPREP Bowel Prep Kit for patients at increased risk of arrhythmias (e.g., patients with a history of prolonged QT, uncontrolled arrhythmias, recent myocardial infarction, unstable angina, congestive heart failure, or cardiomyopathy). Consider pre-dose and post-colonoscopy ECGs in patients at increased risk of serious cardiac arrhythmias.

5.3 Seizures

There have been reports of generalized tonic-clonic seizures and/or loss of consciousness associated with use of bowel preparation products in patients with no prior history of seizures. The seizure cases were associated with electrolyte abnormalities (e.g., hyponatremia, hypokalemia, hypocalcemia, and hypomagnesemia) and low serum osmolality. The neurologic abnormalities resolved with correction of fluid and electrolyte abnormalities.

Use caution when prescribing SUPREP Bowel Prep Kit for patients with a history of seizures and in patients at increased risk of seizure, such as patients taking medications that lower the seizure threshold (e.g., tricyclic antidepressants), patients withdrawing from alcohol or benzodiazepines, or patients with known or suspected hyponatremia [see Drug Interactions (7.1)].

5.4 Use in Patients with Risk of Renal Injury

Use SUPREP Bowel Prep Kit with caution in patients with impaired renal function or patients taking concomitant medications that may affect renal function (such as diuretics, angiotensin converting enzyme inhibitors, angiotensin receptor blockers, or non-steroidal anti-inflammatory drugs) [see Drug Interactions (7.1)]. These patients may be at risk for renal injury. Advise these patients of the importance of adequate hydration with SUPREP Bowl Prep Kit and consider performing baseline and post-colonoscopy laboratory tests (electrolytes, creatinine, and BUN) in these patients [see Use in Specific Populations (8.6)].

5.5 Colonic Mucosal Ulcerations and Ischemic Colitis

Osmotic laxative products may produce colonic mucosal aphthous ulcerations, and there have been reports of more serious cases of ischemic colitis requiring hospitalization. Concurrent use of stimulant laxatives and SUPREP Bowel Prep Kit may increase these risks [see Drug Interactions (7.3)]. Consider the potential for mucosal ulcerations resulting from the bowel preparation when interpreting colonoscopy findings in patients with known or suspect inflammatory bowel disease (IBD).

5.6 Use in Patients with Significant Gastrointestinal Disease

If gastrointestinal obstruction or perforation is suspected, perform appropriate diagnostic studies to rule out these conditions before administering SUPREP Bowel Prep Kit [see Contraindications (4)].

Use with caution in patients with severe active ulcerative colitis.

5.7 Aspiration

Patients with impaired gag reflex or other swallowing abnormalities are at risk for regurgitation or aspiration of SUPREP Bowel Prep Kit solution. Observe these patients during administration of SUPREP Bowel Prep Kit solution. Use with caution in these patients.

5.8 Hypersensitivity Reactions

Serious hypersensitivity reactions, including anaphylaxis, angioedema, dyspnea, rash, pruritus and urticaria have been reported with SUPREP [see Adverse Reactions (6.2)]. Inform patients of the signs and symptoms of anaphylaxis and instruct them to seek immediate medical care should signs and symptoms occur.

6 ADVERSE REACTIONS

The following important adverse reactions for bowel preparations are described elsewhere in the labeling:

- Serious Fluid and Serum Chemistry Abnormalities [see Warnings and Precautions (5.1)]
- Cardiac Arrhythmias [see Warnings and Precautions (5.2)]
- Seizures [see Warnings and Precautions (5.3)]
- Use in Patients with Risk of Renal Injury [see Warnings and Precautions (5.4)]
- Colonic Mucosal Ulceration and Ischemic Colitis [see Warnings and Precautions (5.5)]
- Patients with Significant Gastrointestinal Disease [see Warnings and Precautions (5.6)]
- Aspiration [see Warnings and Precautions (5.7)]
- Hypersensitivity Reactions [see Warnings and Precautions (5.8)]

6.1 Clinical Trials Experience

Because clinical studies are conducted under widely varying conditions, adverse reaction rates observed in the clinical studies of a drug cannot be directly compared to rates in clinical studies of another drug and may not reflect the rates observed in practice.

Adults

The safety of SUPREP Bowel Prep Kit was evaluated in a multi-center, randomized, active controlled trial in 379 adult patients undergoing colonoscopy [see Clinical Studies (14)].

Most Common Adverse Reactions

Table 1 shows the most common adverse reactions reported in at least 2% of patients receiving SUPREP Bowel Prep Kit or the control (a bowel prep containing polyethylene glycol and electrolytes (PEG + E)) administered in split-dose (2-day) regimens.

Table 1: Common Adverse Reactions* in Adult Patients Undergoing Colonoscopy in a Randomized, Active Controlled Trial
Symptom |  | Split-Dose (2-Day) Regimen
Symptom | SUPREP Bowel Prep Kit % N=190 |  | PEG + E product % N=189
Overall Discomfort | 54 |  | 67
Abdominal Distension | 40 |  | 52
Abdominal Pain | 36 |  | 43
Nausea | 36 |  | 33
Vomiting | 8 |  | 4

* reported in at least 2% of patients

Laboratory Abnormalities
Table 2 shows the most common laboratory abnormalities (at least 10% in either treatment group and more than 2% difference between groups) for patients who developed new abnormalities of important electrolytes and uric acid after completing the bowel preparation with either SUPREP Bowel Prep Kit or PEG+E administered as a split-dose (2-day) regimen.

Table 2: Adult Patients with Normal Baseline Serum Chemistry with A Shift to an Abnormal Value While on the Split-Dose (2-Day) Regimen^1
 |  | Day of Colonoscopy N (%)^2 | Day 30 N (%)^2
Bicarbonate (low) | SUPREP | 20 (13) | 7 (4)
 | PEG + Electrolytes | 24 (15) | 4 (3)
Bilirubin, total (high) | SUPREP | 14 (9) | 0 (0)
 | PEG + Electrolytes | 20 (12) | 3 (2)
BUN (high) | SUPREP | 2 (2) | 14 (11)
 | PEG + Electrolytes | 4 (3) | 19 (15)
Calcium (high) | SUPREP | 16 (10) | 8 (5)
 | PEG + Electrolytes | 6 (4) | 6 (4)
Chloride (high) | SUPREP | 4 (2) | 6 (4)
 | PEG + Electrolytes | 20 (12) | 6 (4)
Osmolality (high) | SUPREP | 8 (6) | NA
 | PEG + Electrolytes | 19 (13) | NA
Uric acid (high) | SUPREP | 27 (24) | 13 (12)
 | PEG + Electrolytes | 12 (10) | 20 (17)

^1 The study was not designed to support comparative claims for the laboratory abnormalities reported in this table.

^2 Percent (n/N) of patients where N=number of patients with normal baseline who had abnormal values at the timepoint(s) of interest.

Less Common Adverse Reactions

AV Block (1 case) and CK increase.
Adverse Reactions with Unapproved Use

In another study of 408 adult patients, higher rates of the following adverse reactions and laboratory abnormalities were reported in patients treated with SUPREP Bowel Prep Kit as an evening-only (1-day) regimen compared to the split-dose (2-day) regimen.

- overall discomfort, abdominal distention, nausea, and vomiting
- total bilirubin (high), BUN (high), creatinine (high), osmolality (high), potassium (high) and uric acid (high)

Administration of SUPREP Bowel Prep Kit in an evening-only (1-day) dosing regimen is not recommended.
Pediatrics 12 Years to 16 Years of Age

The safety of SUPREP Bowel Prep Kit was evaluated in a single dose-ranging clinical trial of 89 pediatric patients aged 12 years to 16 years [see Clinical Studies (14)]. In 26 pediatric patients who received SUPREP Bowel Prep Kit (two 4.5-ounce doses), the most common adverse reactions (> 10%) were nausea, abdominal pain, abdominal bloating, and vomiting.

6.2 Postmarketing Experience

The following adverse reactions have been identified during post-approval use of SUPREP. Because these reactions are reported voluntarily from a population of uncertain size, it is not always possible to reliably estimate their frequency or establish a causal relationship to drug exposure.

Hypersensitivity: anaphylaxis, angioedema, dyspnea, rash, pruritus, urticaria [see Warning and Precautions (5.8)]

7 DRUG INTERACTIONS

7.1 Drugs That May Increase Risks of Fluid and Electrolyte Abnormalities

Use caution when prescribing SUPREP Bowel Prep Kit to patients taking medications that increase the risk of fluid and electrolyte disturbances or may increase the risk of adverse events of seizure, arrhythmias, and prolonged QT in the setting of fluid and electrolyte abnormalities [see Warnings and Precautions (5.1, 5.2, 5.3, 5.4)].

7.2 Potential for Reduced Drug Absorption

SUPREP Bowel Prep Kit can reduce the absorption of other co-administered drugs [see Dosage and Administration (2.1)].

- Administer oral medications at least one hour before starting each dose of SUPREP Bowel Prep Kit.
- Administer tetracycline and fluoroquinolone antibiotics, iron, digoxin, chlorpromazine, and penicillamine at least 2 hours before and not less than 6 hours after administration of SUPREP Bowel Prep Kit to avoid chelation with magnesium.

7.3 Stimulant Laxatives

Concurrent use of stimulant laxatives and SUPREP Bowel Prep Kit may increase the risk of mucosal ulceration or ischemic colitis. Avoid use of stimulant laxatives (e.g., bisacodyl, sodium picosulfate) while taking SUPREP Bowel Prep Kit [see Warnings and Precautions (5.5)].

8 USE IN SPECIFIC POPULATIONS

8.1 Pregnancy

Risk Summary
There are no available data on SUPREP Bowel Prep Kit use in pregnant women to evaluate for a drug-associated risk of major birth defects, miscarriage, or adverse maternal or fetal outcomes. Animal reproductive studies have not been conducted with sodium sulfate, potassium sulfate, and magnesium sulfate (SUPREP Bowel Prep Kit).

The estimated background risk of major birth defects and miscarriage for the indicated population is unknown. All pregnancies have a background risk of birth defect, loss, or other adverse outcomes. In the U.S. general population, the estimated background risk of major birth defects and miscarriage in clinically recognized pregnancies is 2% to 4% and 15% to 20%, respectively.

8.2 Lactation

Risk Summary
There are no data available data on the presence of SUPREP Bowel Prep Kit in human or animal milk, the effects on the breastfed child, or the effects on milk production. The developmental and health benefits of breastfeeding should be considered along with the mother’s clinical need for SUPREP Bowel Prep Kit and any potential adverse effects on the breastfed child from SUPREP Bowel Prep Kit or from the underlying maternal condition.

8.4 Pediatric Use

The safety and effectiveness of SUPREP Bowel Prep Kit (two 4.5-ounce doses) have been established for cleansing of the colon as a preparation for colonoscopy in pediatric patients 12 years of age and older. Use of SUPREP Bowel Prep Kit in this age group is supported by evidence from an adequate and well-controlled trial of SUPREP Bowel Prep Kit in adults and a single, dose-ranging, controlled trial in 89 pediatric patients 12 years to 16 years of age [see Clinical Studies (14)]. In the pediatric trial, SUPREP Bowel Prep Kit (two 6-ounce doses) did not demonstrate additional treatment benefit and more patients reported gastrointestinal adverse reactions compared to SUPREP Bowel Prep Kit (two 4.5-ounce doses). Therefore, SUPREP Bowel Prep Kit (two 6-ounce doses) is not recommended for pediatric patients 12 years of age and older [see Dosage and Administration (2.3)]. The safety profile of SUPREP Bowel Prep Kit (two 4.5-ounce doses) in this pediatric population was similar to that seen in adults [see Adverse Reactions (6.1)].

The safety and effectiveness of SUPREP Bowel Prep Kit in pediatric patients less than 12 years of age have not been established.

8.5 Geriatric Use

Of the 375 patients who received SUPREP Bowel Prep Kit in clinical trials, 94 (25%) were 65 years of age or older, and 25 (7%) were 75 years of age or older. No overall differences in safety or effectiveness of SUPREP Bowel Prep Kit, administered as the recommended split-dose (2-day) regimen, were observed between geriatric patients and younger patients. Geriatric patients reported more vomiting when SUPREP Bowel Prep Kit was given as a one-day preparation (not a recommended regimen). Elderly patients are more likely to have decreased hepatic, renal or cardiac function and may be more susceptible to adverse reactions resulting from fluid and electrolyte abnormalities [see Warnings and Precautions (5.1)].

8.6 Renal Impairment

Use SUPREP Bowel Prep Kit with caution in patients with renal impairment or patients taking concomitant medications that may affect renal function. These patients may be at risk for renal injury. Advise these patients of the importance of adequate hydration before, during and after use of SUPREP Bowel Prep Kit and consider performing baseline and post-colonoscopy laboratory tests (electrolytes, creatinine, and BUN) in these patients [see Warnings and Precautions (5.4)].

10 OVERDOSAGE

Overdosage of more than the recommended dose of SUPREP Bowel Prep Kit may lead to severe electrolyte disturbances, as well as dehydration and hypovolemia, with signs and symptoms of these disturbances. [see Warnings and Precautions (5.1, 5.2, 5.3)]. Monitor for fluid and electrolyte disturbances and treat symptomatically.

11 DESCRIPTION

SUPREP Bowel Prep Kit (sodium sulfate, potassium sulfate, and magnesium sulfate) oral solution (for adults) is an osmotic laxative and is provided as two bottles each containing 6 ounces of solution. Each bottle contains: 17.5 grams sodium sulfate, 3.13 grams potassium sulfate, and 1.6 grams magnesium sulfate. Inactive ingredients include: citric acid USP, flavoring ingredients, malic acid FCC, sodium benzoate, NF, sucralose, purified water, USP.

SUPREP Bowel Prep Kit (sodium sulfate, potassium sulfate, and magnesium sulfate) oral solution (for pediatric patients 12 years of age and older) is an osmotic laxative and is provided as two bottles each containing 4.5 ounces of solution. Each bottle contains: 13.13 grams sodium sulfate, 2.35 grams potassium sulfate, and 1.2 grams magnesium sulfate. Inactive ingredients include: citric acid USP, flavoring ingredients, malic acid FCC, sodium benzoate, NF, sucralose, purified water, USP.

Sodium Sulfate, USP

The chemical name is Na2SO4. The average Molecular Weight is 142.04. The structural formula is:

Potassium Sulfate, FCC, purified

The chemical name is K2SO4. The average Molecular Weight is 174.26. The structural formula is:

Magnesium Sulfate, USP

The chemical name is MgSO4. The average Molecular Weight: 120.37. The structural formula is:

Each SUPREP Bowel Prep Kit also contains a polypropylene mixing container.

12 CLINICAL PHARMACOLOGY

12.1 Mechanism of Action

Sulfate salts provide sulfate anions, which are poorly absorbed. The osmotic effect of unabsorbed sulfate anions and the associated cations causes water to be retained within the gastrointestinal tract.

12.2 Pharmacodynamics

No formal pharmacodynamic studies have been conducted with SUPREP Bowel Prep Kit.

12.3 Pharmacokinetics

Absorption and Elimination

After administration of SUPREP Bowel Prep Kit in six healthy subjects, the time at which serum sulfate reached its highest point (Tmax) was approximately 17 hours after the first dose or approximately 5 hours after the second dose, and then declined with a half-life of 8.5 hours.

Excretion

Fecal excretion was the primary route of sulfate elimination.

Specific Populations

Patients with Renal Impairment

The disposition of sulfate after ingestion of SUPREP Bowel Prep Kit was studied in patients (N=6) with moderate renal impairment (creatinine clearance of 30 to 49 mL/min). In patients with moderate renal impairment, mean AUC was 54% higher and mean Cmax was 44% higher, than healthy subjects.

The mean sulfate concentrations in healthy subjects and in patients with moderate renal impairment returned to their respective baselines by Day 6 after dose initiation. Urinary excretion of sulfate over 30 hours after the first dose was approximately 16% lower in patients with moderate renal impairment than in healthy subjects. These differences are not considered clinically meaningful.

Patients with Hepatic Impairment

The disposition of sulfate after ingestion of SUPREP Bowel Prep Kit was studied in patients (N=6) with mild to moderate hepatic impairment (Child-Pugh grades A and B). Systemic exposure of serum sulfate (AUC and Cmax) was similar between healthy subjects and patients with hepatic impairment. The mean sulfate concentrations in healthy subjects and in patients with mild to moderate hepatic impairment returned
to their respective baselines by Day 6 after dose initiation. Urinary excretion of sulfate over 30 hours after the first dose was similar between patients with hepatic impairment and healthy subjects.

13 NONCLINICAL TOXICOLOGY

13.2 Animal Toxicology and/or Pharmacology

The sulfate salts of sodium, potassium, and magnesium contained in SUPREP Bowel Prep Kit were administered orally (gavage) to rats and dogs up to 28 days up to a maximum daily dose of 5 grams/kg/day (approximately 0.9 and 3 times for rats and dogs, respectively, the recommended human dose of 44 grams/day or 0.89 grams/kg based on the body surface area). In rats, the sulfate salts caused diarrhea and electrolyte and metabolic changes, including hypochloremia, hypokalemia, hyponatremia, lower serum osmolality, and high serum bicarbonate. Significant renal changes included increased fractional sodium excretion, increased urinary sodium and potassium excretion, and alkaline urine in both males and females. In addition, creatinine clearance was significantly decreased in females at the highest dose. No microscopic renal changes were seen. In dogs, the sulfate salts caused emesis, excessive salivation, excessive drinking of water, and abnormal excreta (soft and/or mucoid feces and/or diarrhea) and increased urine pH and sodium excretion.

14 CLINICAL STUDIES

Adults

The colon cleansing efficacy of SUPREP Bowel Prep Kit was evaluated in a randomized, single-blind, active-controlled, multicenter study in adult patients scheduled to have a colonoscopy. There were 363 adult patients included in the efficacy analysis. Patients ranged in age from 20 to 84 years (mean age 55 years) and 54% were female. Race distribution was 86% Caucasian, 9% African-American, and 5% other.

Patients were randomized to one of the following two colon preparation regimens: SUPREP Bowel Prep Kit or a marketed polyethylene glycol (PEG) plus electrolytes bowel preparation. In the Study SUPREP Bowel Prep Kit was administered as a split-dose (two-day) regimen. The PEG bowel prep was also given as a split-dose preparation according to its labeled instructions. Patients receiving SUPREP Bowel Prep Kit were limited to a light breakfast followed by clear liquids on the day prior to the day of colonoscopy; patients receiving the PEG bowel prep were allowed to have a normal breakfast and a light lunch, followed by clear liquids.

The primary efficacy endpoint was the proportion of patients with successful colon cleansing as assessed by the colonoscopists, who were not informed about the type of preparation received, as shown in Table 3. In the study, no clinically or statistically significant differences were seen between the group treated with SUPREP Bowel Prep Kit and the group treated with the PEG bowel prep.

Table 3: Proportion of Adult Patients with Successful Colon Cleansing Response Rates
Treatment Group | Regimen | N | Responders^1 % (95% C. I.) | SUPREP – PEG Difference (95% CI)
SUPREP Bowel Prep Kit (with light breakfast) | Split-Dose | 180 | 97% (94%, 99%) | 2%^2 (-2%, 5%)
PEG bowel prep (with normal breakfast & light lunch) | Split-Dose | 183 | 96% (92%, 98%) | 2%^2 (-2%, 5%)

^1 Responders were patients whose colon preparations were graded excellent (no more than small bits of adherent feces/fluid)
or good (small amounts of feces or fluid not interfering with the exam) by the colonoscopist.

^2 Does not equal difference in tabled responder rates due to rounding effects.

Pediatric Patients 12 Years to 16 Years of Age

SUPREP Bowel Prep Kit was evaluated for colon cleansing in a randomized, single-blind, multicenter, doseranging, active-controlled study in 89 pediatric patients 12 years to 16 years of age. The majority of patients were female (57%), white (78%), and of non-Hispanic or non-Latino ethnicity (91%). The mean age was 14 years. The median body weight was 60 kg (range 32 to 155 kg).

Patients were randomized to SUPREP Bowel Prep Kit (two 6-ounce doses), SUPREP Bowel Prep Kit (two 4.5-ounce doses) or oral PEG solution. SUPREP Bowel Prep Kit (two 6-ounce doses) did not demonstrate additional treatment benefit and more patients reported gastrointestinal adverse reactions compared to SUPREP Bowel Prep Kit (two 4.5-ounce doses); therefore, SUPREP Bowel Prep Kit (two 6-ounce doses) is not recommended for pediatric patients 12 years of age and older [see Dosage and Administration (2.4)].

Patients in the SUPREP Bowel Prep Kit (two 4.5-ounce doses) group took the preparation in a “split-dose” regimen, where the first dose was taken the evening before colonoscopy, with the second dose taken the morning of the exam. Patients in the control group took the preparation according to its approved labeling on the evening before colonoscopy.

Patients in the SUPREP Bowel Prep Kit group (two 4.5-ounce doses) were allowed to have a light breakfast on the day before colonoscopy, followed by clear liquids until the colonoscopy is completed the following day. Patients in the control group subjects were permitted only clear liquids on the day prior to colonoscopy until completion of the colonoscopy the following day.

The primary efficacy endpoint was the proportion of patients with successful colon cleansing as assessed by the colonoscopists, who were not informed about the type of preparation received.

The percentage of responders and the associated 95% confidence intervals for the SUPREP Bowel Prep Kit (two 4.5-ounce doses) and Oral PEG solution are shown in Table 4. Efficacy was similar between patients who weighed 65 kg or more (n=12) and those patients who weighed less than 65 kg (n=15) in the SUPREP Bowel Prep Kit (two 4.5-ounce doses) arm.

Table 4: Proportion of Pediatric Patients 12 Years to 16 Years of Age with Successful Colon Cleansing Response Rates
Treatment Group | Regimen | N | Responders^1 % (95% C. I.) | SUPREP – PEG Difference (95% CI)
SUPREP Bowel Prep Kit 4.5 ounces per dose (with light breakfast) | Split-Dose | 26 | 85% (71%, 99%) | 25%^2 (3%, 47%)
Oral PEG solution (with clear liquids only) | Evening Dosing | 32 | 59% (42%, 76%) | 25%^2 (3%, 47%)

^1 Responders were patients whose colon preparations were graded excellent (no more than small bits of adherent feces/fluid) or good (small amounts of feces or fluid not interfering with the exam) by the colonoscopist.

^2 Does not equal difference in tabled responder rates due to rounding effects.

16 HOW SUPPLIED/STORAGE AND HANDLING

Each SUPREP Bowel Prep Kit (sodium sulfate, potassium sulfate, and magnesium sulfate) oral solution (for adults) (NDC 52268-012-01) contains:

- Two bottles (NDC 52268-011-01) each containing 6-ounces of an oral solution of 17.5 grams sodium sulfate, 3.13 grams potassium sulfate, and 1.6 grams magnesium sulfate as a clear to slightly hazy liquid. When diluted as directed, the solution is clear and colorless.
- One (1) mixing container with a 16-ounce fill line.

Each SUPREP Bowel Prep Kit (sodium sulfate, potassium sulfate, and magnesium sulfate) oral solution (for pediatric patients 12 years of age and older) (NDC 52268-112-01) contains:

- Two bottles (NDC 52268-111-01) each containing 4.5-ounces of an oral solution of 13.13 grams sodium sulfate, 2.35 grams potassium sulfate, and 1.2 grams magnesium sulfate as a clear to slightly hazy liquid. When diluted as directed, the solution is clear and colorless.
- One (1) mixing container with a 12-ounce fill line.

STORAGE AND HANDLING

Store at 20° to 25°C (68° to 77°F). Excursions permitted between 15° to 30°C (59° to 86°F). See USP controlled room temperature.

17 PATIENT COUNSELING INFORMATION

Advise the patient and/or caregiver to read the FDA-approved patient labeling (Medication Guide).

Instruct patients or caregivers:

- Must dilute SUPREP Bowel Prep Kit before ingestion.
- Must consume additional water after each dose of SUPREP Bowel Prep Kit.
- On the day before colonoscopy, consume only a light breakfast or clear liquids (e.g., water, apple or orange juice without pulp, lemonade, coffee, tea, or chicken broth). On the day of the colonoscopy only consume clear liquids up to two hours prior to colonoscopy.
- Two doses of SUPREP Bowel Prep Kit are required for a complete preparation for colonoscopy. One bottle of SUPREP Bowel Prep Kit is equivalent to one dose.
- Do not to take other laxatives while taking SUPREP Bowel Prep Kit.
- Do not eat solid food or drink milk or eat or drink anything colored red or purple.
- Do not drink alcohol.
- Do not take oral medications within one hour of starting each dose of SUPREP Bowel Prep Kit.
- If taking tetracycline or fluoroquinolone antibiotics, iron, digoxin, chlorpromazine, or penicillamine, take these medications at least 2 hours before and not less than 6 hours after administration of SUPREP Bowel Prep Kit [see Drug Interactions (7.2)].
- Stop consumption of all fluids at least 2 hours prior to colonoscopy.
- Contact their healthcare provider if they develop significant vomiting or signs of dehydration after taking SUPREP Bowel Prep Kit or if they experience cardiac arrhythmias or seizures [see Warnings and Precautions (5.1, 5.2, 5.3)].
- Seek immediate medical care should signs or symptoms of a hypersensitivity reaction occur [see Warnings and Precautions (5.8)].

Manufactured by Braintree Laboratories, Inc.
Braintree, MA 02185

Please see www.sebelapharma.com for patent information.

MEDICATION GUIDE

SUPREP®(Soo-prep) Bowel Prep Kit
(sodium sulfate, potassium sulfate and magnesium sulfate)
oral solution

Read and understand this Medication Guide at least 2 days before your colonoscopy and again before you start taking SUPREP Bowel Prep Kit.

What is the most important information I should know about SUPREP Bowel Prep Kit?
SUPREP Bowel Prep Kit and other bowel preparations can cause serious side effects, including:

- Serious loss of body fluid (dehydration) and changes in blood salts (electrolytes) in your blood. These changes can cause:

o abnormal heartbeats that can cause death.
o seizures. This can happen even if you have never had a seizure.
o kidney problems.
Your chance of having fluid loss and changes in body salts with SUPREP Bowel Prep Kit is higher if you:

- have heart problems
- have kidney problems
- take water pills or non-steroidal anti-inflammatory drugs (NSAIDS)

Tell your healthcare provider right away if you have any of these symptoms of a loss of too much body fluid (dehydration) while taking SUPREP Bowel Prep Kit:
o vomiting o urinating less often than normal
o dizziness o headache
See "What are the possible side effects of SUPREP Bowel Prep Kit?" for more information about side effects.

What is SUPREP Bowel Prep Kit?
SUPREP Bowel Prep Kit is a prescription medicine used by adults and children 12 years of age and older to clean the colon before a colonoscopy. SUPREP Bowel Prep Kit cleans your colon by causing you to have diarrhea. Cleaning your colon helps your healthcare provider see the inside of your colon more clearly during your colonoscopy.
It is not known if SUPREP Bowel Prep Kit is safe and effective in children under 12 years of age.

Do not take SUPREP Bowel Prep Kit if your healthcare provider has told you that you have:
• a blockage in your intestine (bowel obstruction).
• an opening in the wall of your stomach or intestine (bowel perforation).
• a very dilated intestine (toxic megacolon).
• problems with the emptying of food and fluid from your stomach (gastric retention).
• an allergy to any of the ingredients in SUPREP Bowel Prep Kit. See the end of this Medication Guide for a complete list of ingredients in
SUPREP Bowel Prep Kit.

Before taking SUPREP Bowel Prep Kit, tell your healthcare provider about all of your medical conditions, including if you:
• have problems with serious loss of body fluid (dehydration) and changes in blood salts (electrolytes).
• have gout.
• have heart problems including an irregular heartbeat, especially a condition called "QT prolongation".
• have a history of seizures or take medicines for seizures.
• are withdrawing from drinking alcohol or from taking benzodiazepines.
• have a low blood salt (sodium) level.
• have kidney problems or take medicines for kidney problems.
• have stomach or bowel problems including ulcerative colitis.
• have problems with swallowing or gastric reflux.
• are pregnant or plan to become pregnant. It is not known if SUPREP Bowel Prep Kit will harm your unborn baby. Talk to your healthcare
provider if you are pregnant.
• are breastfeeding or plan to breastfeed. It is not known if SUPREP Bowel Prep Kit passes into your breast milk. You and your healthcare
provider should decide if you will take SUPREP Bowel Prep Kit while breastfeeding.
Tell your healthcare provider about all the medicines you take, including prescription and over-the-counter medicines, vitamins, and herbal supplements.
SUPREP Bowel Prep Kit may affect how other medicines work. Medicines taken by mouth may not be absorbed properly when taken within 1 hour before the start of each dose of SUPREP Bowel Prep Kit.
Especially tell your healthcare provider if you take:
• medicines for blood pressure or heart problems.
• medicines for kidney problems.
• medicines for seizures.
• water pills (diuretics).
• non-steroidal anti-inflammatory medicines (pain medicines).
• medicines for depression or mental health problems.
• laxatives. Do not take other laxatives while taking SUPREP Bowel Prep Kit.
The following medicines should be taken at least 2 hours before starting SUPREP Bowel Prep Kit and not less than 6 hours after taking SUPREP Bowel Prep Kit:
• tetracycline
• fluoroquinolone antibiotics
• iron
• digoxin (Lanoxin)
• chloropromazine
• penicillamine (Cuprimine, Depen)
Ask your healthcare provider or pharmacist for a list of these medicines if you are not sure if you are taking any of the medicines listed above.
Know the medicines you take. Keep a list of them to show your healthcare provider and pharmacist when you get a new medicine.

How should I take SUPREP Bowel Prep Kit?
See the Instructions for Use in the Patient Instructions for Use Booklet for dosing instructions. You must read, understand, and follow these instructions to take SUPREP Bowel Prep Kit the right way.
• Take SUPREP Bowel Prep Kit exactly as your healthcare provider tells you to take it.
• Each bottle of SUPREP Bowel Prep Kit must be mixed with water (diluted) before drinking.
• It is important for you to drink the additional prescribed amount of water listed in the Instructions for Use to prevent fluid loss
(dehydration).
• One bottle of SUPREP Bowel Prep Kit is equal to one dose.
• Two doses of SUPREP Bowel Prep Kit are required for complete colonoscopy preparation.
• All people taking SUPREP Bowel Prep Kit should follow these general instructions starting 1 day before your colonoscopy:
• eat only a light breakfast or clear liquids (for example: water, strained fruit juice without pulp, lemonade, plain coffee, or tea, chicken
broth, gelatin dessert without fruit) on the day before your procedure.
• only drink clear liquids the rest of the day and the next day until 2 hours before your colonoscopy. Stop drinking all fluids at least 2
hours before your colonoscopy.
• after taking SUPREP Bowel Prep Kit if you have any bloating or feeling like your stomach is upset, wait to take your second dose until
your stomach feels better.
• While taking SUPREP Bowel Prep Kit, do not:
• take any other laxatives.
• take any medicines by mouth (oral) within 1 hour of starting SUPREP Bowel Prep Kit.
• eat solid foods, drink dairy (such as milk), or drink alcohol while taking SUPREP Bowel Prep Kit and until after your colonoscopy.
• eat or drink anything colored red or purple.
Contact your healthcare provider right away if after taking SUPREP Bowel Prep Kit you have severe vomiting, signs of dehydration, changes in consciousness such as feeling confused, delirious or fainting (loss of consciousness) or seizures.

What are the possible side effects of SUPREP Bowel Prep Kit?
SUPREP Bowel Prep Kit can cause serious side effects, including:
• See "What is the most important information I should know about SUPREP Bowel Prep Kit?"
• Changes in certain blood tests. Your healthcare provider may do blood tests after you take SUPREP Bowel Prep Kit to check your blood
for changes. Tell your healthcare provider if you have any symptoms of too much fluid loss, including:
o vomiting o nausea o bloating
o dizziness o stomach area (abdomen) cramping o headache
o urinate less than usual o trouble drinking clear liquid o trouble swallowing
o seizures o heart problems o worsening gout
• Ulcers of the bowel or bowel problems (ischemic colitis). Tell your healthcare provider right away if you have severe stomach-area
(abdomen) pain or rectal bleeding.

- Serious allergic reactions. Get medical help right away if you have any signs and symptoms of a serious allergic
  reaction while taking SUPREP Bowel Prep Kit, including:

o difficulty breathing o itching
o swelling of the face, lips, tongue or throat o raised red patches on your skin (hives)
o skin rash
The most common side effects of SUPREP Bowel Prep Kit in adults include:
o overall discomfort o stomach bloating
o stomach pain o nausea
o vomiting
The most common side effects of SUPREP Bowel Prep Kit in children 12 to 16 years of age include:
o nausea o stomach pain
o stomach bloating o vomiting
These are not all the possible side effects of SUPREP Bowel Prep Kit.
Call your doctor for medical advice about side effects. You may report side effects to FDA at 1-800-FDA-1088.

How should I store SUPREP Bowel Prep Kit?
• Store SUPREP Bowel Prep Kit at room temperature, between 68°F to 77°F (20°C to 25°C).
Keep SUPREP Bowel Prep Kit and all medicines out of the reach of children.

General information about the safe and effective use of SUPREP Bowel Prep Kit.
Medicines are sometimes prescribed for purposes other than those listed in a Medication Guide. Do not use SUPREP Bowel Prep Kit for a condition for which it was not prescribed. Do not give SUPREP Bowel Prep Kit to other people, even if they are going to have the same procedure you are. It may harm them. You can ask your pharmacist or healthcare provider for information about SUPREP Bowel Prep Kit that is written for health professionals.

What are the ingredients in SUPREP Bowel Prep Kit?
SUPREP Bowel Prep Kit is supplied in two dosage strengths. SUPREP Bowel Prep Kit comes in a carton containing two 6-ounce bottles, along with a 16-ounce polypropylene mixing container. SUPREP Pediatric Bowel Prep Kit comes in a carton containing two bottles containing 4.5 ounces of
oral solution, along with a 12-ounce polypropylene mixing container.
Each bottle contains:
Active ingredients: sodium sulfate, potassium sulfate and magnesium sulfate.
Inactive ingredients: citric acid, USP, flavoring ingredients, malic acid, FCC, sodium benzoate, NF, sucralose, purified water, USP.
Manufactured by:
Braintree Laboratories, Inc.
270 Centre Street
Holbrook, MA 02343
For more information go to www.sebelapharma.com or call 1-800-874-6756.

This Medication Guide has been approved by the U.S. Food and Drug Administration. Revised 11/2025

Principal Display Panel – Adult Carton Label

NDC 52268-012-01 U.S. Patent 6,946,149

Dispense the enclosed Medication Guide to each patient.

SUPREP
BOWEL PREP KIT
(sodium sulfate, potassium
sulfate and magnesium sulfate)
Oral Solution
For Adults
(17.5g/3.13g/1.6g) per 6 ounces

This carton contains:

2 6-ounce (177 mL) bottles of liquid bowel prep
1 16-ounce mixing container
1 Patient booklet. Booklet includes:
1- Medication Guide
2- Patient Instructions
3- Full Prescribing Information

Recommended Dosage:
See prescribing information

Dilute the solution concentrate as
directed prior to use.

Both 6-ounce bottles are required for
a complete prep.

Rx only

Braintree
A PART OF SEBELA PHARMACEUTICALS

Principal Display Panel – Adult Bottle Label

NDC 52268-011-01

SUPREP
BOWEL PREP KIT
(sodium sulfate, potassium
sulfate and magnesium sulfate)
Oral Solution
For Adults
(17.5g/3.13g/1.6g) per 6 ounces

Dispense the enclosed Medication Guide to each patient.

This bottle contains 6 ounces (177 mL) of liquid bowel prep

Directions:
Dilute the solution concentrate prior to use. See enclosed booklet for
complete dosage and administration instructions. Both 6-ounce
bottles are required for a complete prep.

Keep this and other drugs out of reach of children.
Store at 25°C (77°F); excursions permitted to 15-30°C (59-86°F).

Manufactured by Braintree Laboratories, Braintree, MA Rx only Rev July ‘20

Principal Display Panel – Pediatric Carton Label

NDC 52268-112-01 U.S. Patent 6,946,149

Dispense the enclosed Medication Guide to each patient.

SUPREP®
BOWEL PREP KIT
(sodium sulfate, potassium
sulfate and magnesium sulfate)
Oral Solution
For pediatric patients 12 years of age and older
(13.13g/2.35g/1.2g) per 4.5 ounces

This carton contains:

2 Bottles containing 4.5 ounces
of liquid bowel prep
1 12-ounce mixing container
1 Patient booklet. Booklet includes:
1- Medication Guide
2- Patient Instructions
3- Full Prescribing Information

Recommended Dosage:
See prescribing information

Dilute the solution concentrate as
directed prior to use.

Both bottles containing 4.5 ounces of oral
solutions are required for a complete prep.

Rx only

Braintree
A PART OF SEBELA PHARMACEUTICALS

Principal Display Panel – Pediatric Bottle Label

NDC 52268-111-01

SUPREP®
BOWEL PREP KIT
(sodium sulfate, potassium
sulfate and magnesium sulfate)
Oral Solution
For pediatric patients 12 years of age and older
(13.13g/2.35g/1.2g) per 6 ounces

Dispense the enclosed Medication Guide to each patient.

This bottle contains 4.5 ounces of liquid bowel prep

Directions:
Dilute the solution concentrate prior to use. See enclosed booklet for
complete dosage and administration instructions. Both 6 bottles
containing 4.5 ounces of oral soultion are required for a complete prep.

Keep this and other drugs out of reach of children.
Store at 25°C (77°F); excursions permitted to 15-30°C (59-86°F).

Manufactured by Braintree Laboratories, Braintree, MA Rx only July 2020